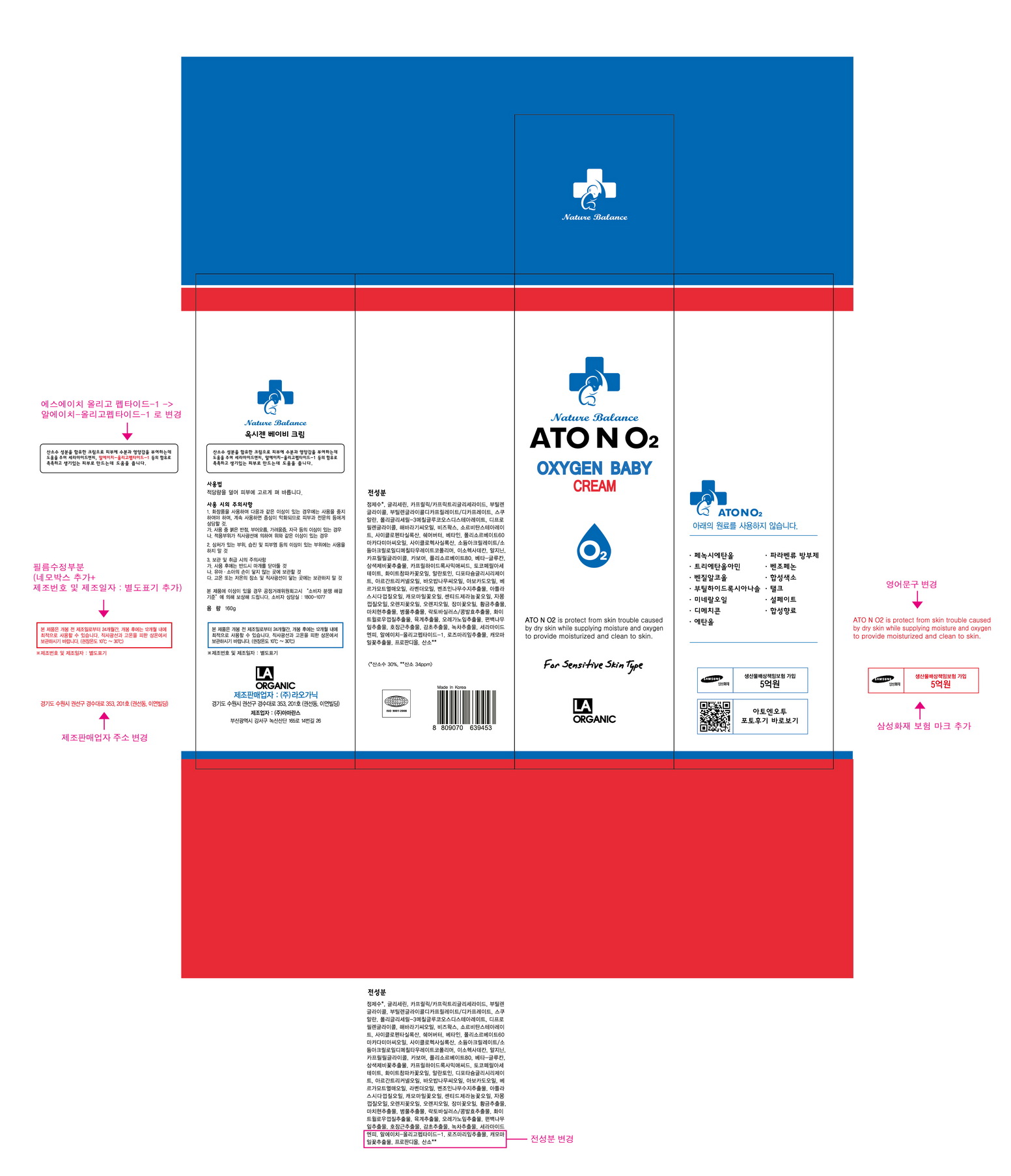 DRUG LABEL: ATONO2 Oxygen Baby Cream
NDC: 70993-0011 | Form: CREAM
Manufacturer: LAORGANIC Co., Ltd.
Category: otc | Type: HUMAN OTC DRUG LABEL
Date: 20161013

ACTIVE INGREDIENTS: GLYCERIN 8.06 g/100 g
INACTIVE INGREDIENTS: SHEA BUTTER; WATER

Drug Facts

ACTIVE INGREDIENT

Glycerin

INACTIVE INGREDIENT

Water, Caprylic/Capric Triglyceride, Butylene Glycol, Butylene Glycol Dicaprylate/Dicaprate, Polyglyceryl-3 Methylglucose Distearate, Squalane, Dipropylene Glycol, Helianthus Annuus (Sunflower) Seed Oil, Beeswax, Cyclopentasiloxane, Sorbitan Stearate, Butyrospermum Parkii (Shea) Butter, Macadamia Integrifolia Seed Oil, Betaine, etc.

PURPOSE

Skin Protectant

keep out of reach of the children

INDICATIONS AND USAGE

Apply proper amount to the skin.

WARNINGS

- For external use only
- When using this product

1. If any one of following symptoms occurs when using cosmetics, stop using it and consult a dermatologist.
A. red spot, swelling, itching, stimulus
B. symptoms mentioned above are caused by sunlight.

2. Do not apply on skin where there is wound, eczema, or irritation.

3. Storage and cautions for handling
A. Close stopper after using.
B. Keep out of reach of children.
C. Keep away from high or low temperature and direct sunlight.

4. This is not a medicinal product. Made of 100% cosmetic ingredients, it is a sensitive-skin care product for all skin types.

DOSAGE AND ADMINISTRATION

for external use only